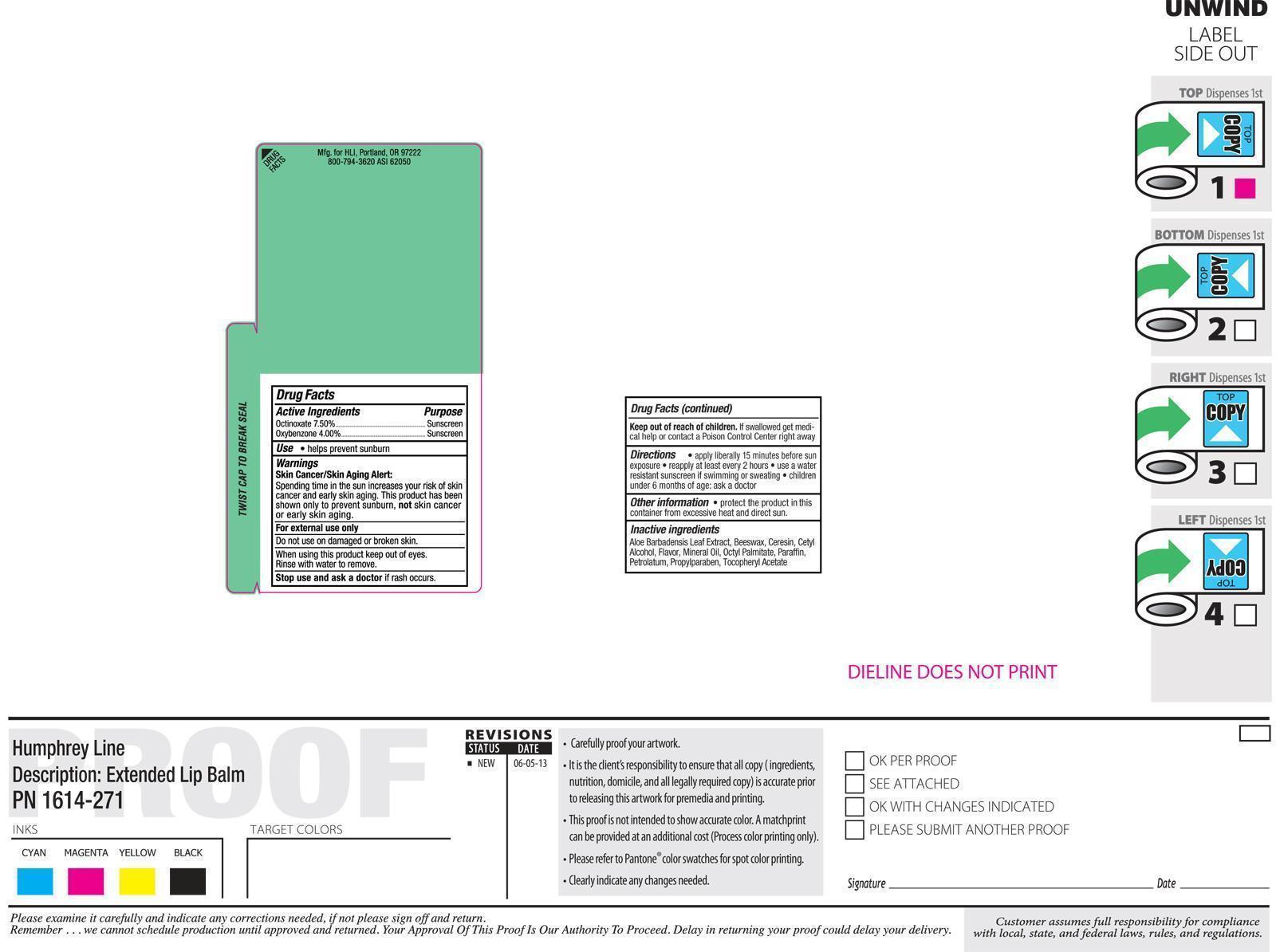 DRUG LABEL: sunscreen
NDC: 19392-300 | Form: LIPSTICK
Manufacturer: Humphreyline
Category: otc | Type: HUMAN OTC DRUG LABEL
Date: 20200101

ACTIVE INGREDIENTS: OCTINOXATE 75 mg/1 g; OXYBENZONE 40 mg/1 g
INACTIVE INGREDIENTS: PETROLATUM; ETHYLHEXYL PALMITATE; YELLOW WAX; PARAFFIN; MINERAL OIL; CERESIN; CETYL ALCOHOL; ALOE VERA LEAF; .ALPHA.-TOCOPHEROL ACETATE; PROPYLPARABEN

Drug Facts

ACTIVE INGREDIENT

Octinoxate (7.5%)

Oxybenzone (4%)

PURPOSE

Sunscreen

INDICATIONS AND USAGE

Helps prevent sunburn and chapped lips

INACTIVE INGREDIENT

Petrolatum, Octyl Palmitate, Beeswax, Paraffin, Mineral Oil, Ceresin, Cetyl Alcohol, Fragrance, Aloe Barbadensis Leaf Extract, Tocopheryl Acetate (Vitamin E), Propylparaben